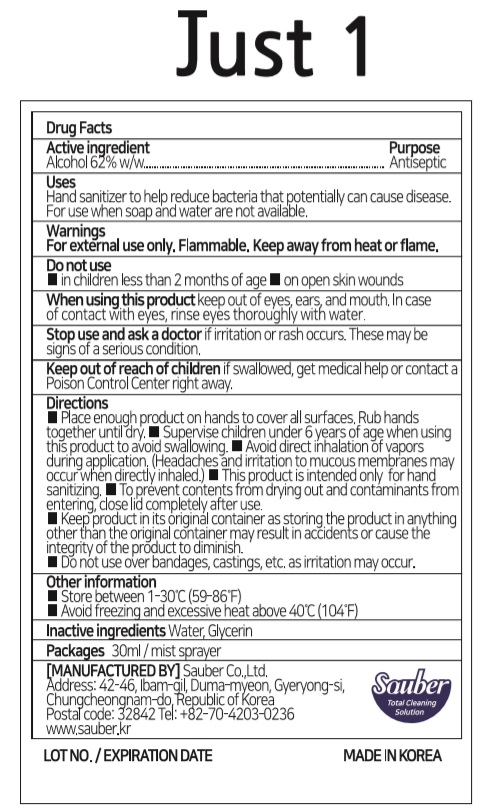 DRUG LABEL: Just 1
NDC: 78880-362 | Form: SPRAY
Manufacturer: Sauber Co.,Ltd.
Category: otc | Type: HUMAN OTC DRUG LABEL
Date: 20200710

ACTIVE INGREDIENTS: ALCOHOL 18.6 mL/30 mL
INACTIVE INGREDIENTS: GLYCERIN; WATER

Just 1 | 30 ml | Mist sprayer